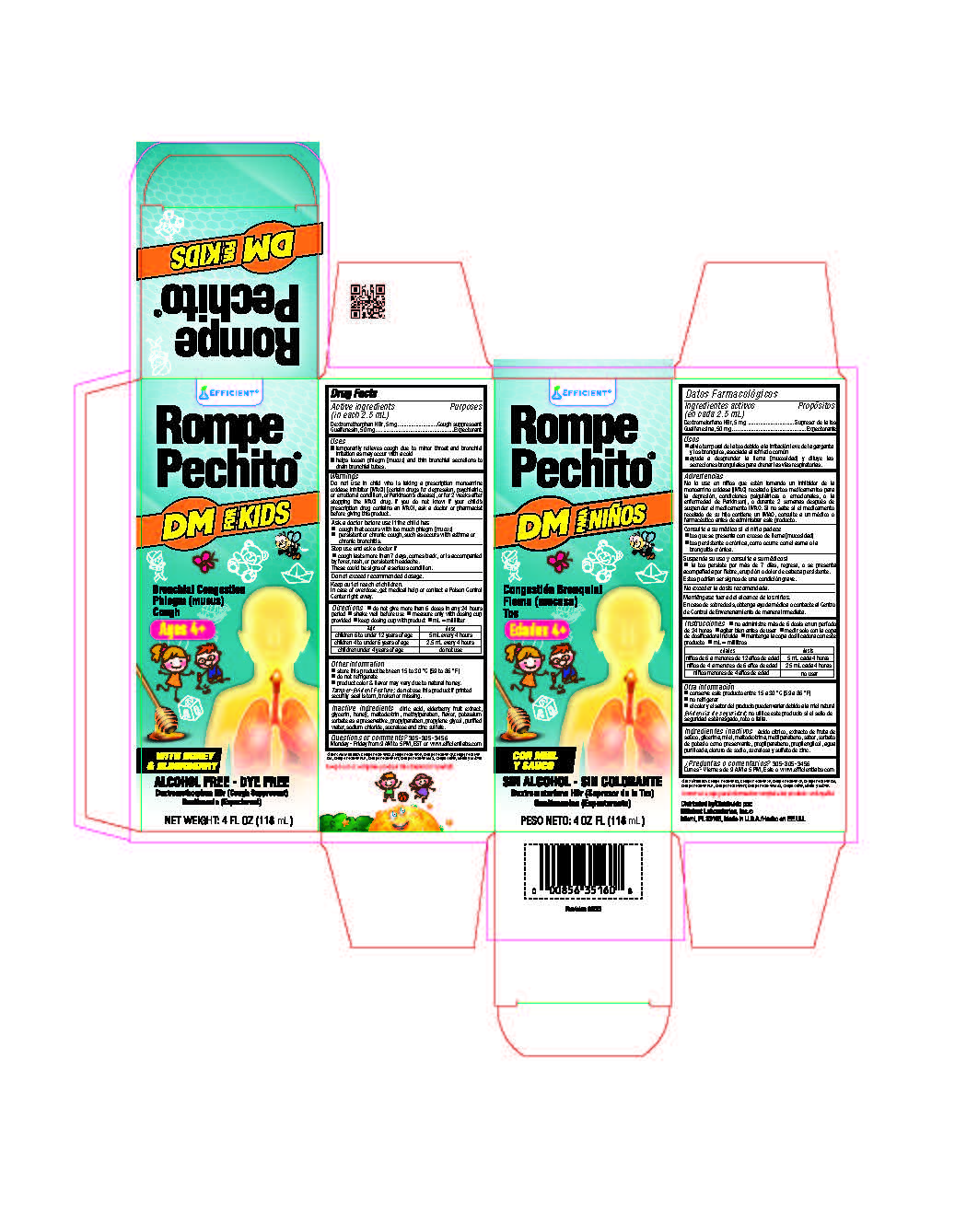 DRUG LABEL: Rompe Pechito
NDC: 58593-276 | Form: LIQUID
Manufacturer: Efficient Laboratories Inc
Category: otc | Type: HUMAN OTC DRUG LABEL
Date: 20251014

ACTIVE INGREDIENTS: DEXTROMETHORPHAN HYDROBROMIDE 5 mg/2.5 mL; GUAIFENESIN 50 mg/2.5 mL
INACTIVE INGREDIENTS: SUCRALOSE; ANHYDROUS CITRIC ACID; AMERICAN ELDERBERRY; MALTODEXTRIN; METHYLPARABEN; HONEY; POTASSIUM SORBATE; PROPYLENE GLYCOL; PROPYLPARABEN; WATER; SODIUM CHLORIDE; ZINC SULFATE; GLYCERIN

Rompe Pechito

ACTIVE INGREDIENT

Active Ingredients:(in each teaspoonful 2.5 ml.) Purpose

Dextromethorphan Hydrobromide 5 mg ...................................... Cough Suppressant

Guaifenesin 50 mg ................................................................... Expectorant

Purpose

Cough Suppressant

Expectorant

Uses

- temporarily relieves cough due to minor throat and bronchial irritation as may occur with a cold
- helps loosen phlegm (mucus) and thin bronchial secretions to drain bronchial tubes.

Warnings

Do not use in child who is taking a prescription monoamine oxidase inhibitor (MAOI) (certain drugs for depression, psychiatric, or emotional condition, or Parkinson’s disease), or for 2 weeks after stopping the MAOI drug. If you do not know if your child’s prescription drug contains an MAOI, ask a doctor or pharmacist before giving this product.

Do not use in child who is taking a prescription monoamine oxidase inhibitor (MAOI) (certain drugs for depression, psychiatric, or emotional condition, or Parkinson’s disease), or for 2 weeks after stopping the MAOI drug. If you do not know if your child’s prescription drug contains an MAOI, ask a doctor or pharmacist before giving this product.

Keep out of reach of children.

In case of overdose, get medical help or contact a Poison Control Center right away.

Directions

Do not give more than 6 doses in any 24 hours period  shake well before use  measure only with dosing cup provided  keep dosing cup with product  mL = milliliter

Age Dose

Children 6 to under 12 years of age 5 mL every 4 hours

Children 4 to under 6 years of age 2.5 mL every 4 hours

Children under 4 years of age Do not use

Inactive Ingredients:

Inactive Ingredients: citric acid, elderberry fruit extract, glycerin, honey, maltodextrin, methylparaben, flavor, potassium sorbate as a preservative, propylparaben, propylene glycol, purified water, sodium chloride, sucralose and zinc sulfate.

Questions or Comments?

305-805-3456 Monday - Friday 9AM to 5PM EST

www.efficientlabs.com

Stop use and ask a doctor if

 cough that occurs with too much phlegm (mucus)
 persistent or chronic cough, such as occurs with asthma or chronic bronchitis.

These could be signs of a serious condition.

Ask a doctor before use if the child has

- cough that occurs with too much phlegm (mucus)
- persistent or chronic cough, such as occurs with asthma or chronic bronchitis

Other Information

- store this product between 15 to 30 °C (59 to 86 °F)
- do not refrigerate
- product color & flavor may vary due to natural honey
  Tamper-Evident Feature: do not use this product if printed security seal is torn, broken or missing.